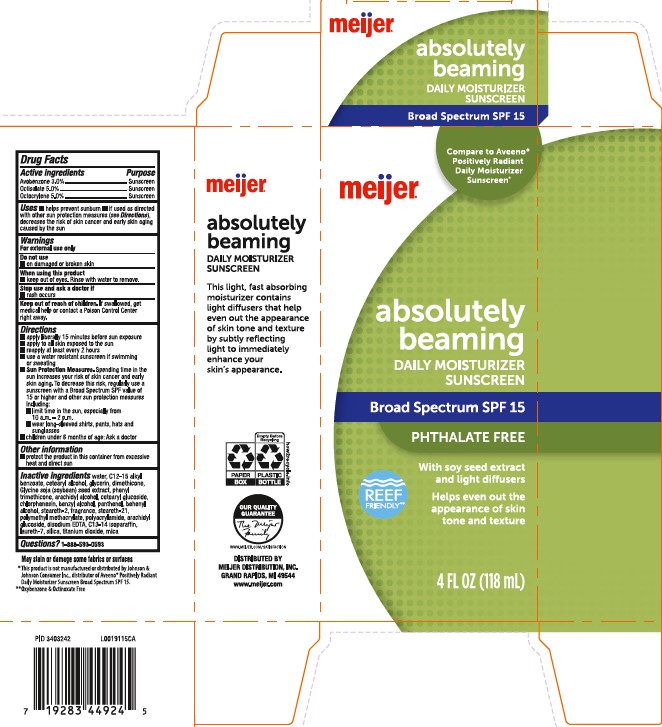 DRUG LABEL: daily moisturizer
NDC: 79481-0001 | Form: LOTION
Manufacturer: Meijer, Inc.
Category: otc | Type: HUMAN OTC DRUG LABEL
Date: 20260219

ACTIVE INGREDIENTS: AVOBENZONE 30 mg/1 mL; OCTISALATE 50 mg/1 mL; OCTOCRYLENE 50 mg/1 mL
INACTIVE INGREDIENTS: WATER; ALKYL (C12-15) BENZOATE; CETOSTEARYL ALCOHOL; GLYCERIN; DIMETHICONE; SOYBEAN; PHENYL TRIMETHICONE; ARACHIDYL ALCOHOL; CETEARYL GLUCOSIDE; CHLORPHENESIN; BENZYL ALCOHOL; PANTHENOL; DOCOSANOL; STEARETH-2; STEARETH-21; POLY(METHYL METHACRYLATE; 450000 MW); POLYACRYLAMIDE (10000 MW); ARACHIDYL GLUCOSIDE; EDETATE DISODIUM ANHYDROUS; C13-14 ISOPARAFFIN; LAURETH-7; SILICON DIOXIDE; TITANIUM DIOXIDE; MICA

Meijer 159.000/159AA
Absolutely Beaming Daily Moisturizer SPF 15

active ingredients

Avobenzone 3%

Octisalate 5.0%

Octocrylene 5.0%

Purpose

Sunscreen

Use

- helps prevent sunburn
- if used as directed with other sun protection measures (see Directions), decreases the risk of skin cancer and early skin aging caused by the sun

Warnings

For external use only

Do not use

- on damaged or broken skin

When using this product

- keep out of the eyes. Rinse with water to remove.

stop use and ask a doctor if

- rash occurs

Keep out of reach of children.

If swallowed, get medical help or contact a Poison Control Center right away.

Directions

- apply liberally 15 minures before sun exposure
- apply to all skin exposed to the sun
- reapply at least every 2 hours
- use a water resistant sunscreen if swimming or sweating
- Sun Protecton Measures. Spending time in the sun increases your risk of skin cancer and early skin aging. To decrease this risk, regularly use a sunscreen with a Broad Spectrum SPF value of 15 or higher and other sun protection measures including
- limit time in the sun, especiually from 10 a.m. - 2 p.m.
- wear long-sleeved shirts, pants, hats and sunglasses
- childen under 6 months of age: Ask a doctor

Other information

- protect the product from excessive heat and direct sun

Inactive ingredients

water, C12-15 alkyl benzoate, cetearyl alcohol, glycerin, dimethicone, Glycine soja (soybean) seed extract, phenyl trimethicone, arachidyl alcohol, cetearyl glucoside, chlorphenesin, benzyl alcohol, panthenol, behenyl alcohol, steareth-2, fragrance, steareth-21, polymethyl methacrylate, polyacrylamide, arachidyl glucoside, disodium EDTA, C13-14 isoparaffin, laureth-7, silica, titanium dioxide, mica

Questions?

1-888-593-0593

ADVERSE REACTION

Absolutely Beaming

daily moisturizer

sunscreen

This light, fast absorbing moisturizing contains soy seed extract and lightdiffusers that help even out the appearance of skin tone and texture by subtly reflecting light to immediately enhance your skin's appearance.

PAPER BOX

Empty Before Recycling

PLASTIC BOTTLE

how2recycle.info

OUR QUALITY GUARANTEE

The Meijer Family

WWW.MEIJER.COM/SATISFACTION

DISTRIBUTED BY

MEIJER DISTRIBUTION, INC

GRAND RAPIDS, MI 49544

www.meijer.com

May stain or damage some fabrics or surfaces

* This product is not manufactured or distributed by Johnson & Johnson Consumer Inc., distributor of Aveeno®Postively Radiant Daily Moisturizer Sunscreen Broad spectrum SPF 15

** Oxybenzone & Octinoxate Free

principal display panel

Compare to Aveeno®Positively Radiant Daily Moisturizer Sunscreen*

meijer®

absolutely

beaming

DAILY MOISTURIZER

SUNSCREEN

Broad Spectrum SPF 15

PHTHALATE FREE

With soy seed extract and light diffusers

Helps even out the appearance of skin tone and texture

REEF FRIENDLY**

4 FL OZ (118 mL)